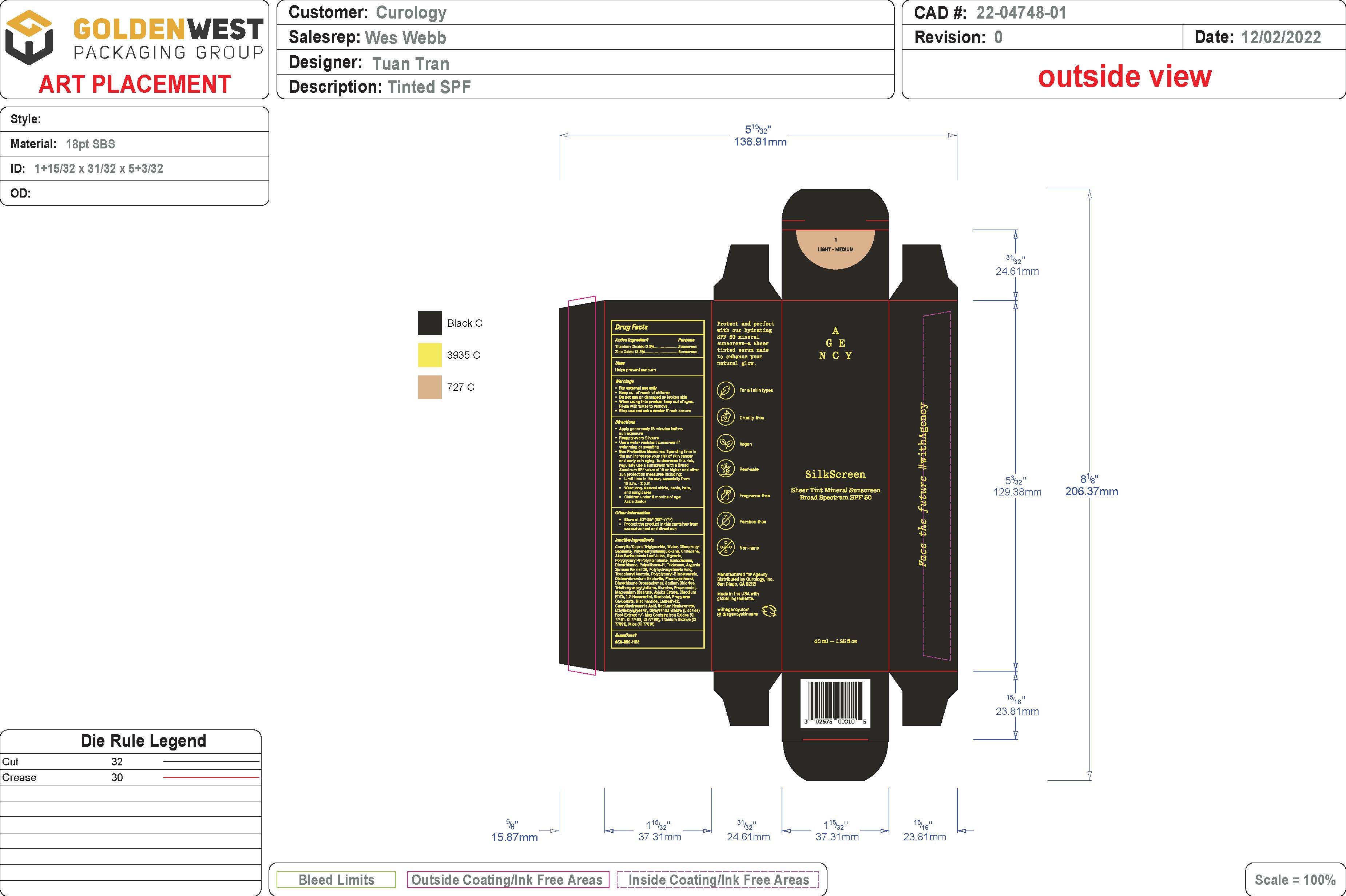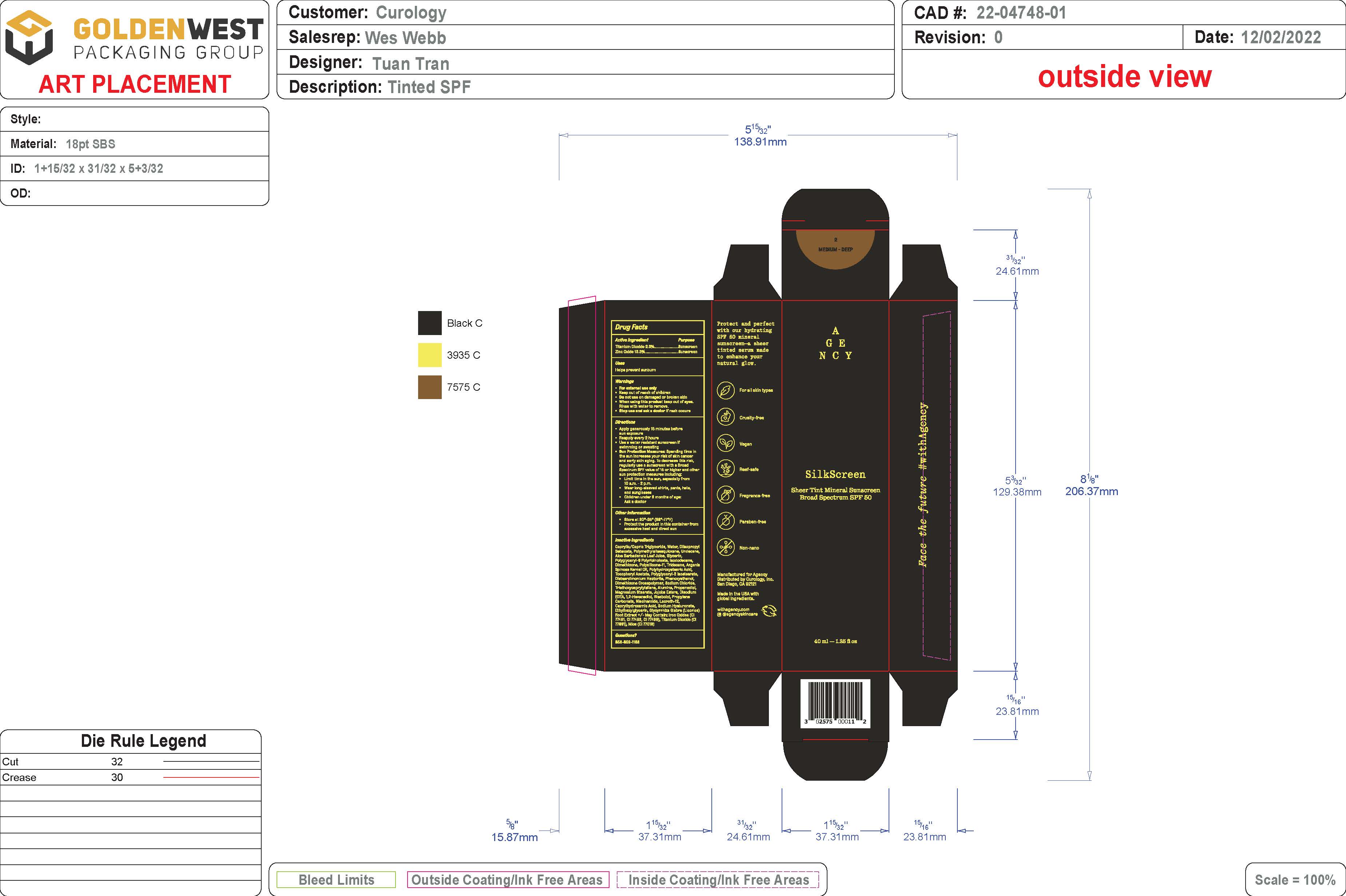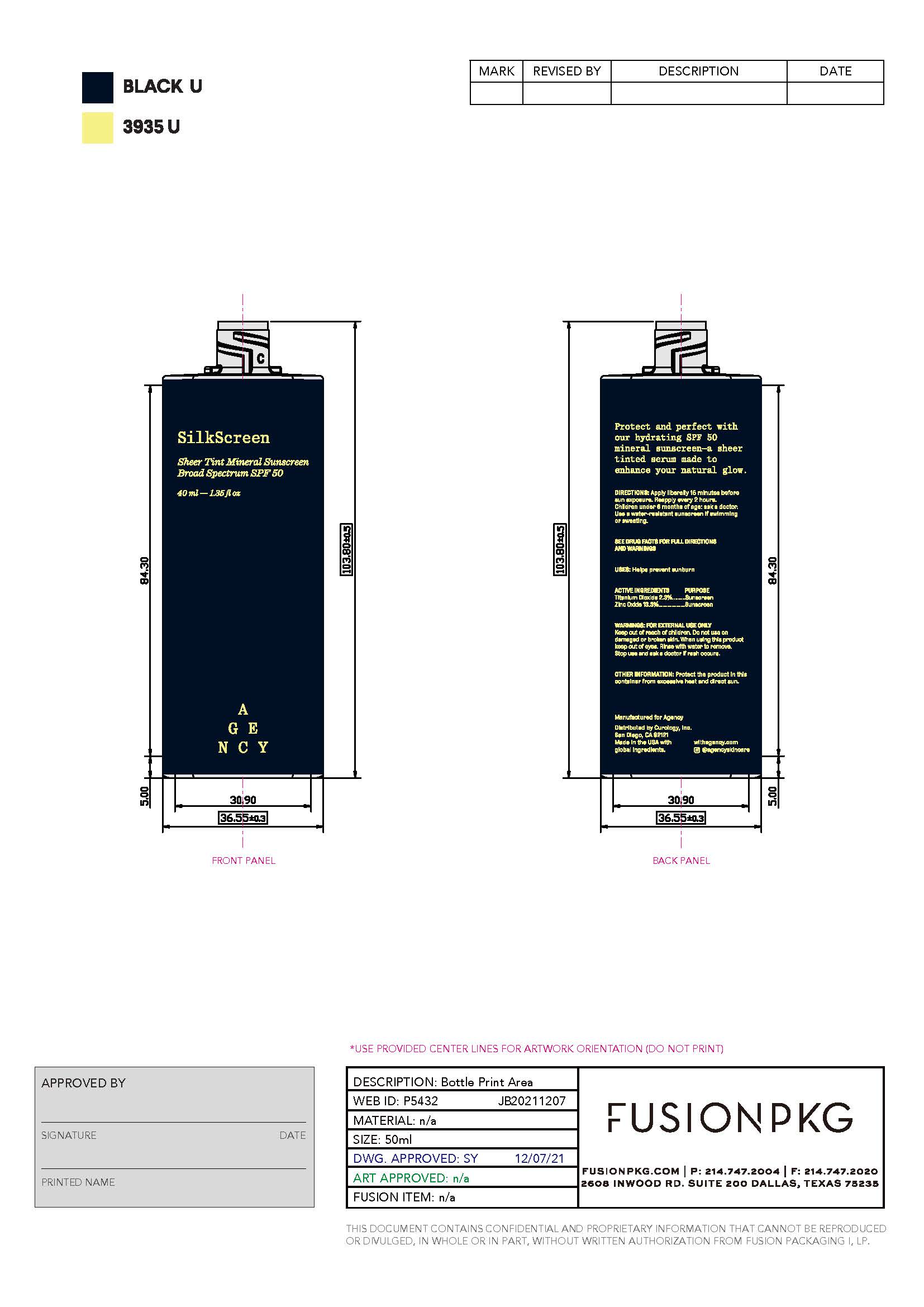 DRUG LABEL: Sheer Tint Mineral Sunscreen Broad Spectrum SPF 50 - Light/Medium Shade
NDC: 51514-0361 | Form: LOTION
Manufacturer: Autumn Harp
Category: otc | Type: HUMAN OTC DRUG LABEL
Date: 20230605

ACTIVE INGREDIENTS: TITANIUM DIOXIDE 2.37 g/100 g; ZINC OXIDE 13.35 g/100 g
INACTIVE INGREDIENTS: LAURETH-12; FERROSOFERRIC OXIDE; HYALURONATE SODIUM; ETHYLHEXYLGLYCERIN; GLYCYRRHIZA GLABRA; DIISOPROPYL SEBACATE; UNDECANE; MEDIUM-CHAIN TRIGLYCERIDES; WATER; POLYMETHYLSILSESQUIOXANE (11 MICRONS); ISODODECANE; MICA; .ALPHA.-TOCOPHEROL ACETATE, DL-; ALUMINUM OXIDE; FERRIC OXIDE YELLOW; JOJOBA OIL; .ALPHA.-BISABOLOL, (+/-)-; .ALPHA.-TOCOPHEROL, DL-; TRIDECANE; POLYHYDROXYSTEARIC ACID (2300 MW); POLYGLYCERYL-2 ISOSTEARATE; PHENOXYETHANOL; SODIUM CHLORIDE; PROPANEDIOL; MAGNESIUM STEARATE; EDETATE DISODIUM; 1,2-HEXANEDIOL; PROPYLENE CARBONATE; NIACINAMIDE; FERRIC OXIDE RED; CYCLOMETHICONE 6; ALOE VERA LEAF; CAPRYLHYDROXAMIC ACID; GLYCERIN; POLYGLYCERYL-6 POLYRICINOLEATE; DIMETHICONE 100; ARGANIA SPINOSA SEED; DISTEARDIMONIUM HECTORITE; DIMETHICONE/VINYL DIMETHICONE CROSSPOLYMER (SOFT PARTICLE); TRIETHOXYCAPRYLYLSILANE

Sheer Tint Mineral Sunscreen Broad Spectrum SPF 50 - Light/Medium Shade

Active Ingredient

Zinc Oxide 13.3%

Titanium Dioxide 2.3%

PURPOSE

Sunscreen

DOSAGE AND ADMINISTRATION

Helps prevent sunburn

WARNINGS

For external use only

Keep out of reach of children. If swallowed get medical help or contact a Poison Control Center right awy

Do not use on damaged or broken skin

When using this product keep out of eyes. Rinse with water to remove.

Stop use and ask a doctor if rash occurs

INSTRUCTIONS FOR USE

Apply generously 15 minutes before sun exposure

Reapply every 2 hours

Use a water resistant sunscreen if swimming or sweating

Sun Protection Measures: Spending time in the sun increases your risk of skin cancer and early skin aging. To decrease this risk, regularly use a sunscreen with a Broad Spectrum SPF value of 15 or higher and other sun protection measures including:

- Limit time in the sun, especially from 10am - 2pm,
- Wear long-sleeved shirts, pants, hats, and sunglasses

Children under 6 months of age: Ask a doctor

OTHER SAFETY INFORMATION

Store at 20-25C (68-77F)

Protect the product in this container from excessive heat and direct sun

INACTIVE INGREDIENT

Caprylic/Capric Triglyceride, Water, Diisopropyl Sebacate, Polymethylsilsesquioxane, Undecane, Aloe Barbadensis Leaf Juice, Glycerin, Polyglyceryl-6 Polyricinoleate, Isododecane, Dimethicone, Mica, Polysilicone-11, Tridecane, Argania Spinosa Kernel Oil, Polyhydroxystearic Acid, Tocopheryl Acetate, Polyglyceryl-2 Isostearate, Disteardimonium Hectorite, Phenoxyethanol, Dimethicone Crosspolymer, Sodium Chloride, Triethoxycaprylylsilane, Alumina, Propanediol, Iron Oxide (CI 77492), Magnesium Stearate, Jojoba Esters, Disodium EDTA, 1,2-Hexanediol, Bisabolol, Propylene Carbonate, Titanium Dioxide (CI 77891), Niacinamide, Iron Oxides (CI 77491), Cyclohexasiloxane, Laureth-12, Caprylhydroxamic Acid, Iron Oxides (Black, CI 77499), Sodium Hyaluronate, Ethylhexylglycerin, Tocopherol, Glycyrrhiza Glabra (Licorice) Root Extract, Iron Oxides (CI77499).

QUESTIONS

888-859-1188

INDICATIONS AND USAGE

Apply generously 15 minutes before sun exposure

Reapply every 2 hours

Use a water resistant sunscreen if swimming or sweating

Sun Protection Measures: Spending time in the sun increases your risk of skin cancer and early skin aging. To decrease this risk, regularly use a sunscreen with a Broad Spectrum SPF value of 15 or higher and other sun protection measures including:

- Limit time in the sun, especially from 10am - 2pm,
- Wear long-sleeved shirts, pants, hats, and sunglasses

Children under 6 months of age: Ask a doctor

Keep out of reach of children. If swallowed get medical help or contact a Poison Control Center right away

PACKAGE LABEL

image components